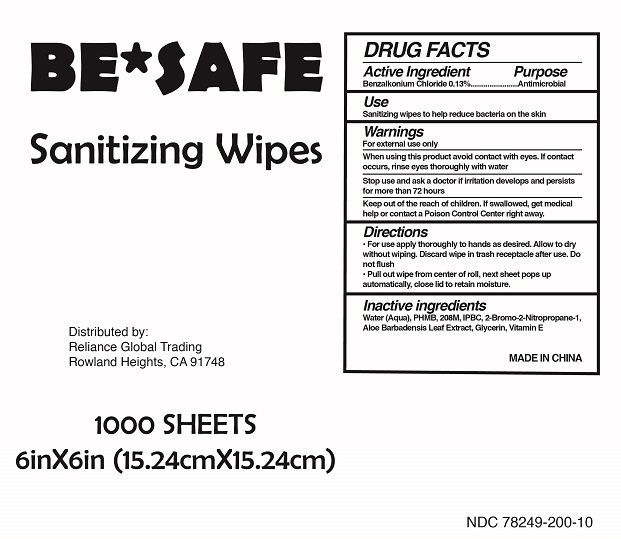 DRUG LABEL: Be Safe Sanitizing Wipes
NDC: 78249-200 | Form: CLOTH
Manufacturer: Reliance Global Trading
Category: otc | Type: HUMAN OTC DRUG LABEL
Date: 20200611

ACTIVE INGREDIENTS: BENZALKONIUM CHLORIDE 0.0013 mg/1 1
INACTIVE INGREDIENTS: WATER; GLYCERIN; IODOPROPYNYL BUTYLCARBAMATE; ALOE VERA LEAF; POLYAMINOPROPYL BIGUANIDE; ALPHA-TOCOPHEROL

Be Safe Sanitizing Wipes

Antiseptic

sanitizine wipes to help reduce bacteria on skin

ACTIVE INGREDIENT

Benzalkonium Chloride 0.13%

INDICATIONS AND USAGE

to decrease bacteria on the skin

Directions

- For use apply thoroughly to hands as desired. Allow to dry without wiping. Discard wipe in trash reciptacle after use. Do not flush.
- Pull out wipe from center of roll, next sheet pops up automatically, close lid to retain moisture.

WARNINGS

For external hands only

KEEP OUT OF REACH OF CHILDREN

In case of accidental ingestion, seek professional assistance or contact a Poison Control Center right away.

INACTIVE INGREDIENT

water, glycerin, polysorbate 20, aloe leaf extract, chamomilla flower extract, sodium benzoate, phenoxethanol, tocopheryl acetate, citric acid

INSTRUCTIONS FOR USE

wipe hands thoroughly with product and allow to dry

keep out of eyes. In case of contact with eyes, flush thoroughly with water.